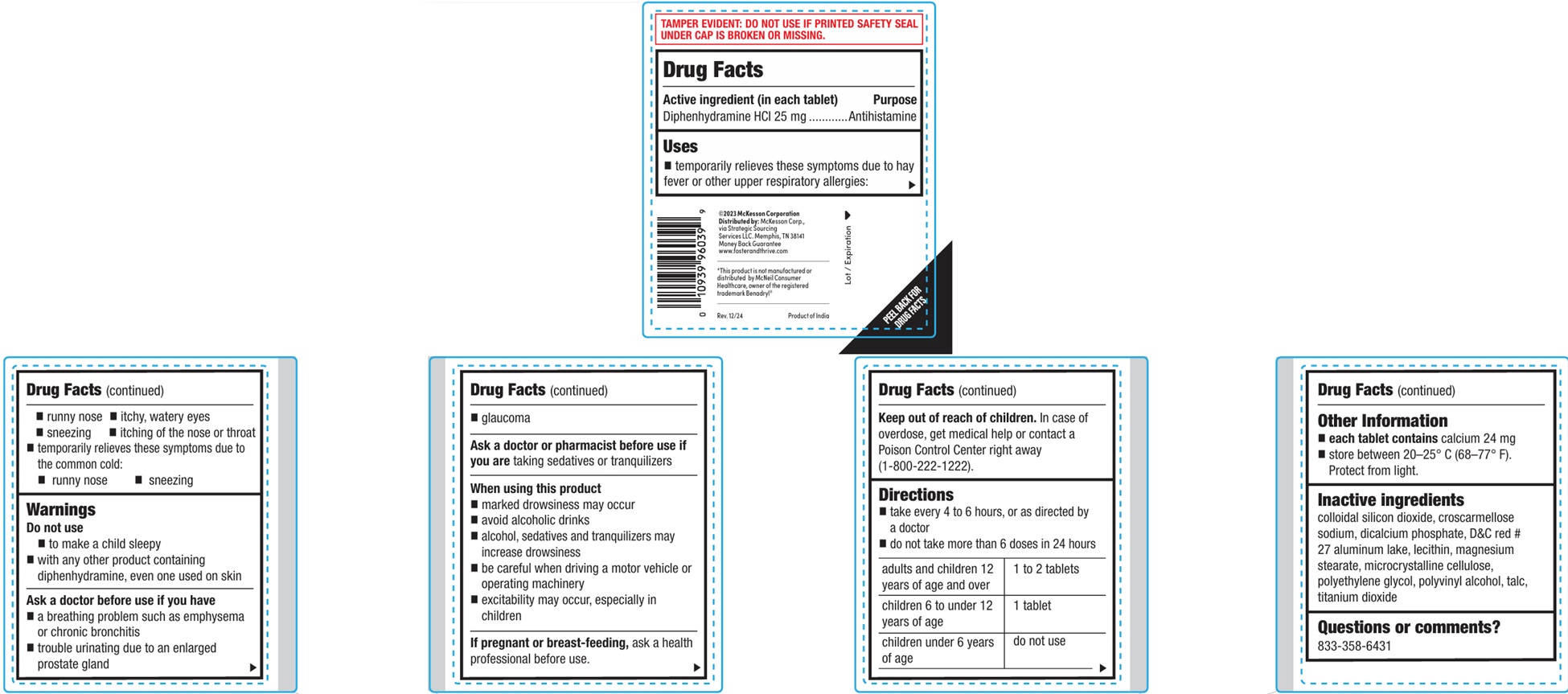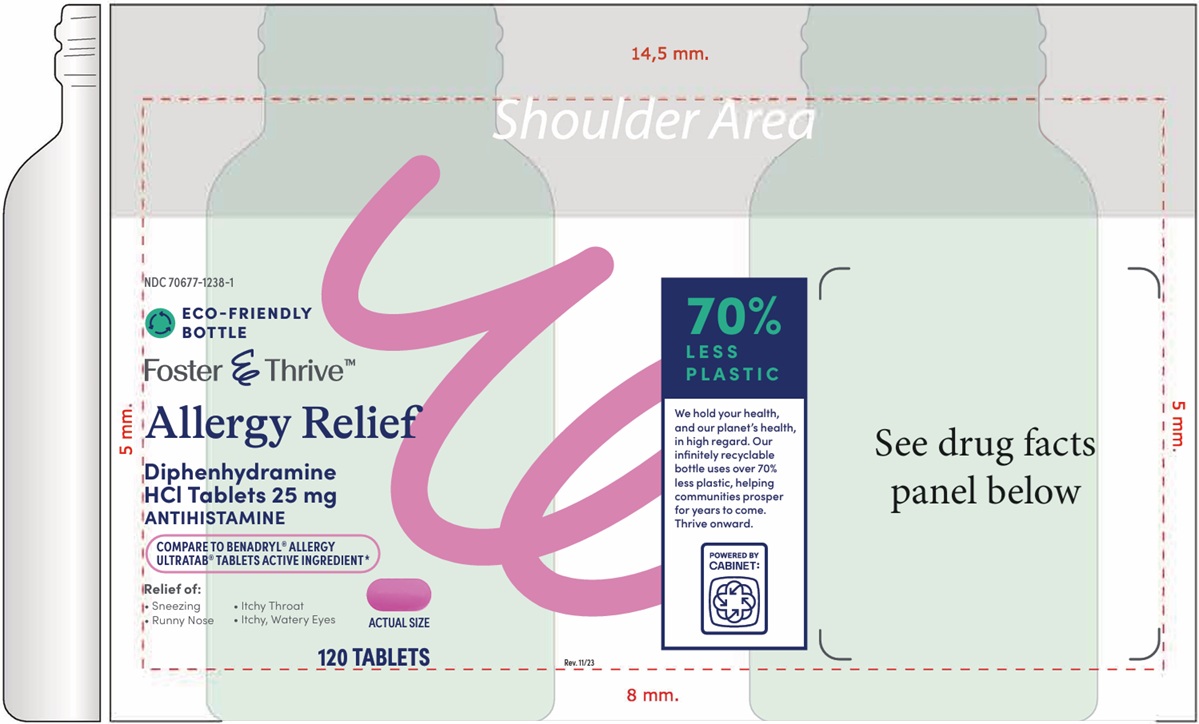 DRUG LABEL: Allergy Relief
NDC: 70677-1238 | Form: TABLET, FILM COATED
Manufacturer: Strategic Sourcing Services, LLC
Category: otc | Type: HUMAN OTC DRUG LABEL
Date: 20260129

ACTIVE INGREDIENTS: DIPHENHYDRAMINE HYDROCHLORIDE 25 mg/1 1
INACTIVE INGREDIENTS: SILICON DIOXIDE; CROSCARMELLOSE SODIUM; ANHYDROUS DIBASIC CALCIUM PHOSPHATE; D&C RED NO. 27 ALUMINUM LAKE; LECITHIN, SOYBEAN; MAGNESIUM STEARATE; MICROCRYSTALLINE CELLULOSE; POLYETHYLENE GLYCOL, UNSPECIFIED; POLYVINYL ALCOHOL, UNSPECIFIED; TALC; TITANIUM DIOXIDE

Allergy Relief